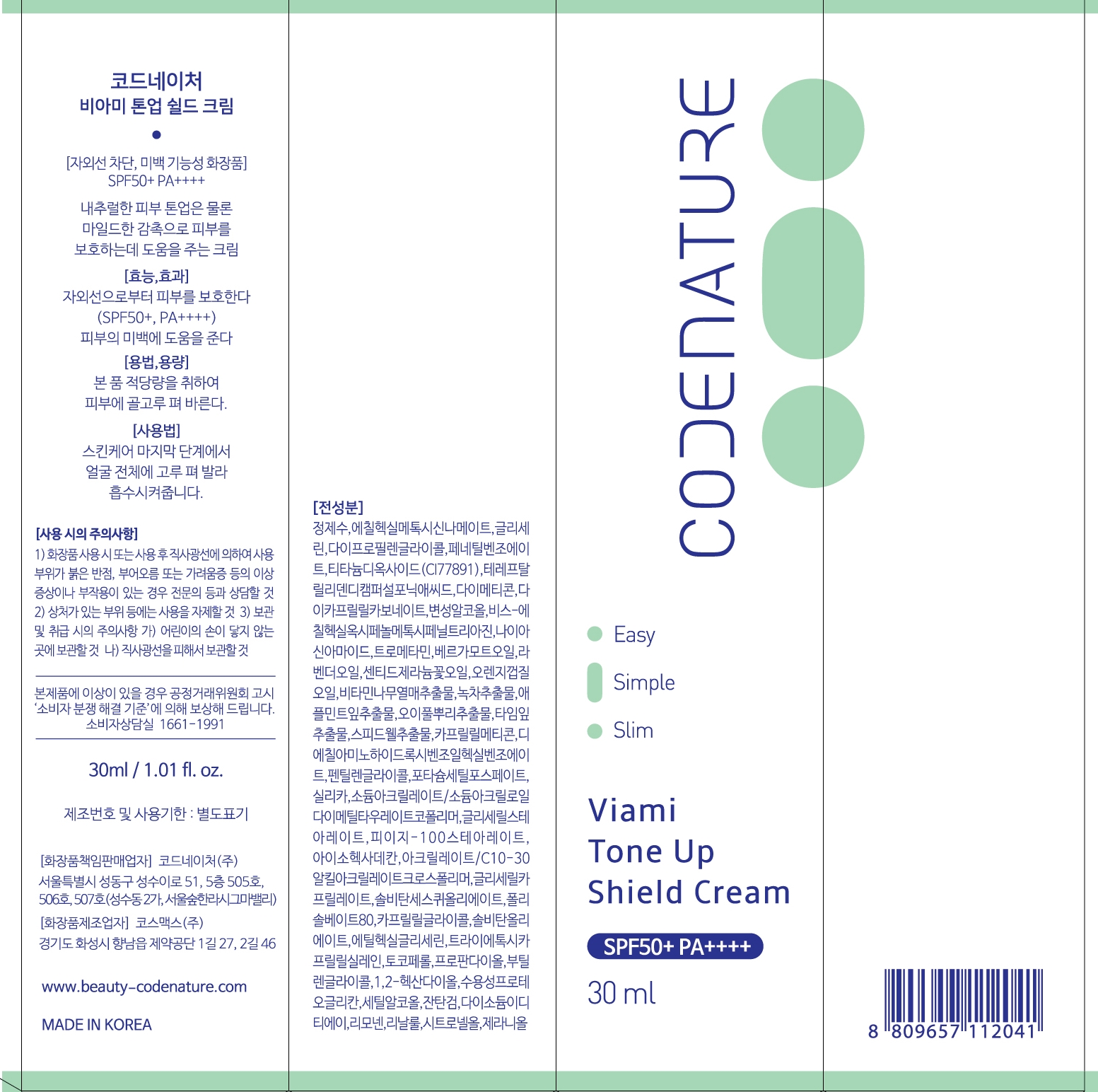 DRUG LABEL: Codenature Viami Tone Up Shield Cream
NDC: 78625-201 | Form: CREAM
Manufacturer: CODENATURE INC
Category: otc | Type: HUMAN OTC DRUG LABEL
Date: 20200620

ACTIVE INGREDIENTS: OCTINOXATE 6800 mg/100 mL; BEMOTRIZINOL 2500 mg/100 mL; TITANIUM DIOXIDE 3950 mg/100 mL
INACTIVE INGREDIENTS: VERONICA OFFICINALIS FLOWERING TOP; WATER; PENTYLENE GLYCOL; PEG-100 STEARATE; TOCOPHEROL; TRIETHOXYCAPRYLYLSILANE; HIPPOPHAE RHAMNOIDES FRUIT; MENTHA X ROTUNDIFOLIA LEAF; CETYL ALCOHOL; SORBITAN SESQUIOLEATE; GLYCERYL CAPRYLATE; CAPRYLYL GLYCOL; BERGAMOT OIL; ETHYLHEXYLGLYCERIN; PELARGONIUM GRAVEOLENS FLOWER OIL; PROPANEDIOL; BUTYLENE GLYCOL; 1,2-HEXANEDIOL; GREEN TEA LEAF; SANGUISORBA OFFICINALIS ROOT; THYMUS VULGARIS LEAF; ISOHEXADECANE; SILICON DIOXIDE; CARBOMER INTERPOLYMER TYPE A (ALLYL SUCROSE CROSSLINKED); POLYSORBATE 80; XANTHAN GUM; SORBITAN MONOOLEATE; ORANGE OIL; LAVENDER OIL; CAPRYLYL TRISILOXANE; SODIUM ACRYLATE/SODIUM ACRYLOYLDIMETHYLTAURATE COPOLYMER (4000000 MW); GLYCERYL MONOSTEARATE; EDETATE DISODIUM ANHYDROUS; GLYCERIN; DICAPRYLYL CARBONATE; DIETHYLAMINO HYDROXYBENZOYL HEXYL BENZOATE; DIPROPYLENE GLYCOL; PHENETHYL BENZOATE; ECAMSULE; DIMETHICONE; ALCOHOL; NIACINAMIDE; TROMETHAMINE; POTASSIUM CETYL PHOSPHATE

Active Ingredients

Ethylhexyl Methoxycinnamate 6.8%

Titanium Dioxide (CI 77891) 3.95%

Bis-Ethylhexyloxyphenol Methoxyphenyl Triazine 2.5%

Purpose

Sunscreen

Uses

Helps prevent sunburn

Warnings

Skin Cancer/Skin Aging Alert : Spending time in the sun increases your

Risk of skin cancer and early skin aging. This product has been shown

Only to prevent sunburn, no skin cancer or early skin aging.

For external use only

Do not use

on damaged or broken skin

When using this product

keep out of eyes

Stop use and ask a doctor

if rash occurs

Keep out of reach of children.

If product is swallowed, get medical

Help or contact a poison Control Center right away.

Directions

Apply liberally 15 minutes before sun exposure

Reapply:

- After 40 minutes of swimming or sweating

- Immediately after towel drying

- At least every 2 hours

Children under 6 months : Ask a doctor

Inactive Ingredients

Glycerin, Dipropylene Glycol, Phenethyl Benzoate, Terephthalylidene Dicamphor Sulfonic Acid,

Dimethicone, Dicaprylyl Carbonate, Alcohol Denat, Niacinamide, Tromethamine, Caprylyl Methicone

Diethylamino Hydroxybenzoyl Hexyl Benzoate, Pentylene Glycol, Potassium Cetyl Phosphate,

Glyceryl Stearate, PEG-100 Stearate, Isohexadecane, Cetyl Alcohol, Sorbitan Sesquioleate, Silica,

Camellia Sinensis Leaf Extract, Thymus Vulgaris (Thyme) Leaf Extract, Water

Other Information

Protect this product from excessive heat and direct sun